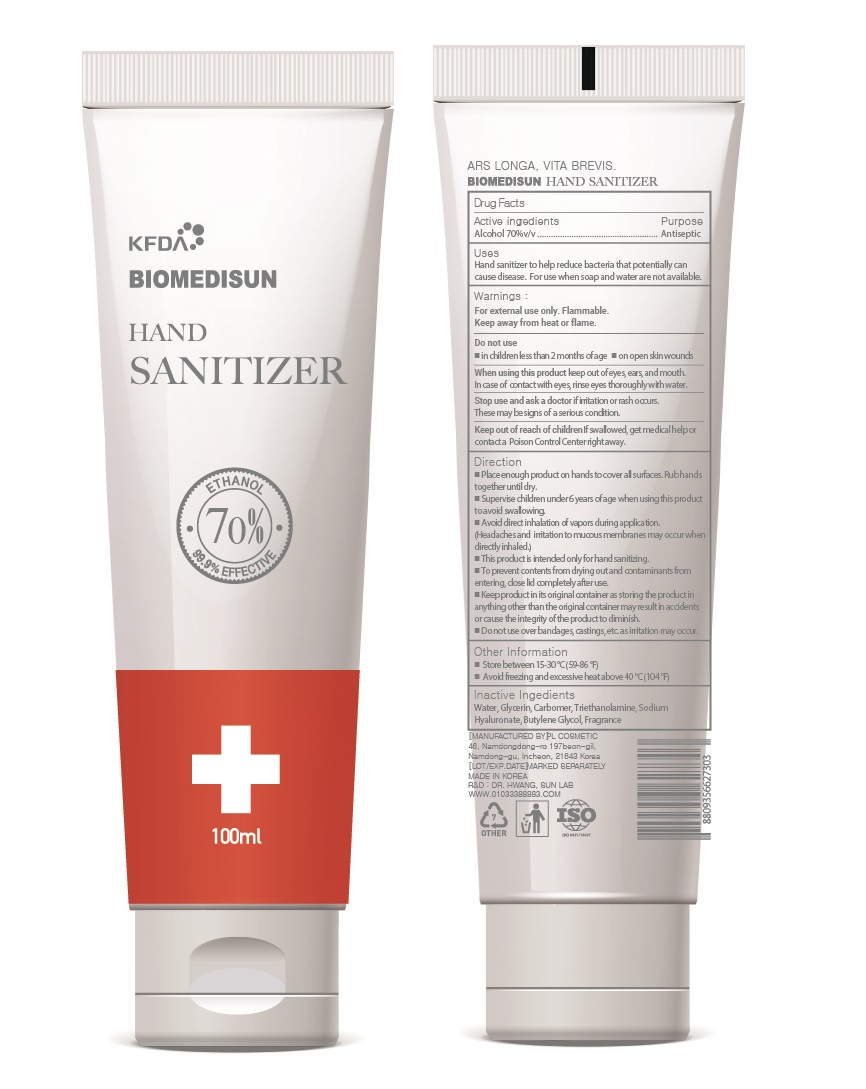 DRUG LABEL: BIOMEDISUN HAND SANITIZER
NDC: 74339-4170 | Form: GEL
Manufacturer: PL COSMETIC
Category: otc | Type: HUMAN OTC DRUG LABEL
Date: 20200406

ACTIVE INGREDIENTS: ALCOHOL 70 mL/100 mL
INACTIVE INGREDIENTS: GLYCERIN; CARBOMER HOMOPOLYMER, UNSPECIFIED TYPE; WATER; BUTYLENE GLYCOL; HYALURONATE SODIUM; TROLAMINE

[BIOMEDISUN] 100 ml TUBE TYPE 70: 74339-4170